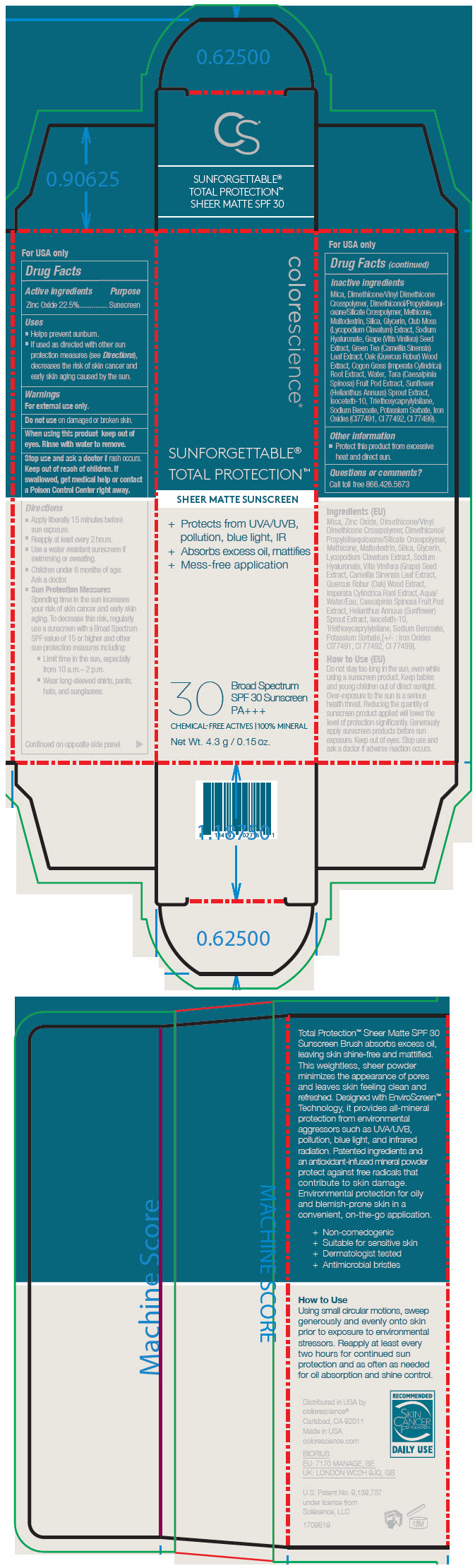 DRUG LABEL: Sunforgettable Total Protection Sheet Matte Sunscreen SPF 30
NDC: 68078-036 | Form: POWDER
Manufacturer: Colorescience
Category: otc | Type: HUMAN OTC DRUG LABEL
Date: 20241216

ACTIVE INGREDIENTS: Zinc Oxide 225 mg/1 g
INACTIVE INGREDIENTS: Mica; DIMETHICONE/VINYL DIMETHICONE CROSSPOLYMER (HARD PARTICLE); DIMETHICONOL/PROPYLSILSESQUIOXANE/SILICATE CROSSPOLYMER (450000000 MW); METHICONE (20 CST); Maltodextrin; SILICON DIOXIDE; Glycerin; Isoceteth-10; HYALURONATE SODIUM; VITIS VINIFERA SEED; GREEN TEA LEAF; QUERCUS ROBUR TWIG BARK; IMPERATA CYLINDRICA ROOT; Water; TARA SPINOSA RESIN; SUNFLOWER OIL; Sodium Benzoate; Potassium Sorbate; Triethoxycaprylylsilane; FERRIC OXIDE YELLOW; FERROSOFERRIC OXIDE; FERRIC OXIDE RED

Sunforgettable® Total Protection™ Sheet Matte Sunscreen SPF 30

Drug Facts

Active ingredients

Zinc Oxide 22.5%

Purpose

Sunscreen

Uses

- Helps prevent sunburn.
- If used as directed with other sun protection measures (see Directions), decreases the risk of skin cancer and early skin aging caused by the sun.

Warnings

For external use only.

Do not use on damaged or broken skin.

When using this product keep out of eyes. Rinse with water to remove.

Stop use and ask a doctor if rash occurs.

Keep out of reach of children. If swallowed, get medical help or contact a Poison Control Center right away.

Directions

- Apply liberally 15 minutes before sun exposure.
- Reapply at least every 2 hours.
- Use a water resistant sunscreen if swimming or sweating.
- Children under 6 months of age: Ask a doctor.
- Sun Protection Measures
  Spending time in the sun increases your risk of skin cancer and early skin aging. To decrease this risk, regularly use a sunscreen with a Broad Spectrum SPF value of 15 or higher and other sun protection measures including:
  - Limit time in the sun, especially from 10 a.m.– 2 p.m.
  - Wear long-sleeved shirts, pants, hats, and sunglasses.

Inactive ingredients

Mica, Dimethicone/Vinyl Dimethicone Crosspolymer, Dimethiconol/Propylsilsequioxane/Silicate Crosspolymer, Methicone, Maltodextrin, Silica, Glycerin, Club Moss (Lycopodium Clavatum) Extract, Sodium Hyaluronate, Grape (Vitis Vinifera) Seed Extract, Green Tea (Camellia Sinensis) Leaf Extract, Oak (Quercus Robur) Wood Extract, Cogon Grass (Imperata Cylindrica) Root Extract, Water, Tara (Caesalpinia Spinosa) Fruit Pod Extract, Sunflower (Helianthus Annuus) Sprout Extract, Isoceteth-10, Triethoxycaprylylsilane, Sodium Benzoate, Potassium Sorbate, Iron Oxides (CI77491, CI 77492, CI 77499).

Other information

- Protect this product from excessive heat and direct sun.

Questions or comments?

Call toll free 866.426.5673

Distributed in USA by
colorescience®
Carlsbad, CA 92011

PRINCIPAL DISPLAY PANEL - 4.3 g Tube Carton

colorescience®

SUNFORGETTABLE®
TOTAL PROTECTION™

SHEER MATTE SUNSCREEN

+ Protects from UVA/UVB,
  pollution, blue light, IR
+ Absorbs excess oil, mattifies
+ Mess-free application

30 Broad Spectrum
SPF 30 Sunscreen
PA+++

CHEMICAL-FREE ACTIVES | 100% MINERAL

Net Wt. 4.3 g / 0.15 oz.